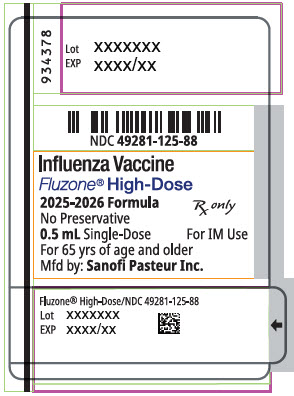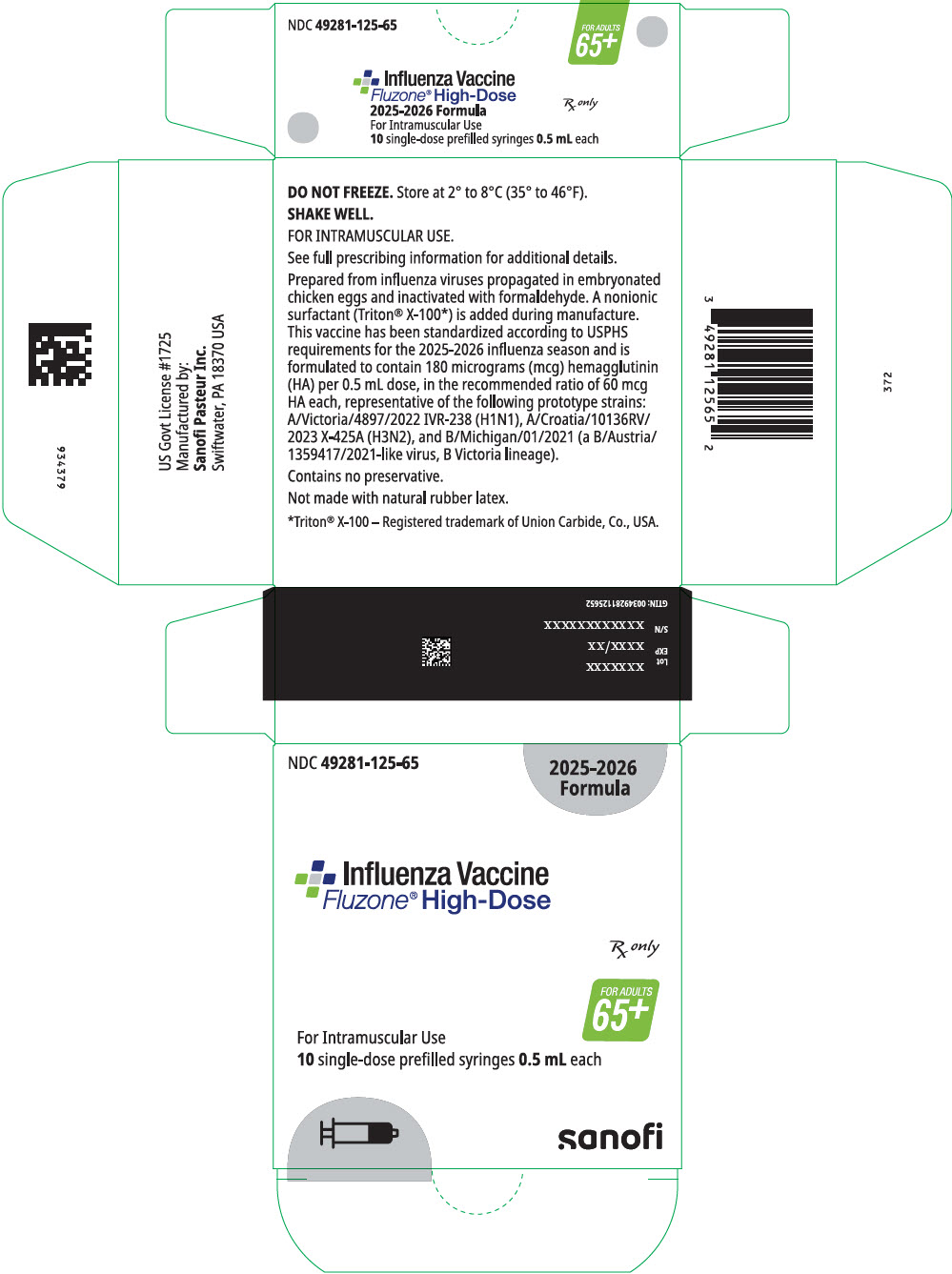 DRUG LABEL: FLUZONE HIGH DOSE NORTHERN HEMISPHERE
NDC: 49281-125 | Form: INJECTION, SUSPENSION
Manufacturer: Sanofi Pasteur Inc.
Category: other | Type: VACCINE LABEL
Date: 20250702

ACTIVE INGREDIENTS: INFLUENZA A VIRUS A/VICTORIA/4897/2022 IVR-238 (H1N1) ANTIGEN (FORMALDEHYDE INACTIVATED) 60 ug/0.5 mL; INFLUENZA A VIRUS A/CROATIA/10136RV/2023 X-425A (H3N2) ANTIGEN (FORMALDEHYDE INACTIVATED) 60 ug/0.5 mL; INFLUENZA B VIRUS B/MICHIGAN/01/2021 ANTIGEN (FORMALDEHYDE INACTIVATED) 60 ug/0.5 mL
INACTIVE INGREDIENTS: SODIUM PHOSPHATE, DIBASIC, ANHYDROUS; SODIUM PHOSPHATE, MONOBASIC, ANHYDROUS; WATER; OCTOXYNOL-9; FORMALDEHYDE

HIGHLIGHTS OF PRESCRIBING INFORMATION

These highlights do not include all the information needed to use Fluzone® High-Dose safely and effectively. See full prescribing information for Fluzone High-Dose.
Fluzone High-Dose (Influenza Vaccine)
injectable suspension, for intramuscular use
2025–2026 Formula
Initial U.S. Approval: 2009

1 INDICATIONS AND USAGE

Fluzone High-Dose is a vaccine indicated for active immunization for the prevention of disease caused by influenza A subtype viruses and type B virus contained in the vaccine. (1)

Fluzone High-Dose is approved for use in persons 65 years of age and older. (1)

2 DOSAGE AND ADMINISTRATION

- For intramuscular use

Administer Fluzone High-Dose as a single 0.5 mL dose. (2)

3 DOSAGE FORMS AND STRENGTHS

Fluzone High-Dose is an injectable suspension. A single dose is 0.5 mL. (3)

4 CONTRAINDICATIONS

Do not administer Fluzone High-Dose to anyone with a history of severe allergic reaction (e.g., anaphylaxis) to any component of the vaccine, including egg protein, or to a previous dose of any influenza vaccine. (4, 11)

5 WARNINGS AND PRECAUTIONS

- If Guillain-Barré Syndrome (GBS) has occurred within 6 weeks following previous influenza vaccination, the decision to give Fluzone High-Dose should be based on careful consideration of the potential benefits and risks. (5.1)

6 ADVERSE REACTIONS

- In adults ≥65 years of age, the most common (>10%) injection-site adverse reaction was pain (>35.6%); the most common solicited systemic adverse reactions were myalgia (21.4%), malaise (18.0%), and headache (16.8%). (6.1)

To report SUSPECTED ADVERSE REACTIONS, contact Sanofi Pasteur Inc., Discovery Drive, Swiftwater, PA 18370 at 1-800-822-2463 (1-800-VACCINE) or VAERS at 1-800-822-7967 or https://vaers.hhs.gov.

FULL PRESCRIBING INFORMATION

1 INDICATIONS AND USAGE

Fluzone® High-Dose is a vaccine indicated for active immunization for the prevention of disease caused by influenza A subtype viruses and type B virus contained in the vaccine.

Fluzone High-Dose is approved for use in persons 65 years of age and older.

2 DOSAGE AND ADMINISTRATION

For intramuscular use

2.1 Dose and Schedule

Administer Fluzone High-Dose as a single 0.5 mL dose from one prefilled syringe.

2.2 Administration

Fluzone High-Dose is a colorless opalescent liquid. Parenteral drug products should be inspected visually for particulate matter and discoloration prior to administration, whenever solution and container permit. If either of these conditions exist, the vaccine should not be administered.

Before administering a dose of vaccine, shake the prefilled syringe.

Administer Fluzone High-Dose intramuscularly.

3 DOSAGE FORMS AND STRENGTHS

Fluzone High-Dose is an injectable suspension.

A single dose is 0.5 mL.

4 CONTRAINDICATIONS

Do not administer Fluzone High-Dose to anyone with a history of severe allergic reaction (e.g., anaphylaxis) to any component of the vaccine [see Description (11)], including egg protein, or to a previous dose of any influenza vaccine.

5 WARNINGS AND PRECAUTIONS

5.1 Guillain-Barré Syndrome

If Guillain-Barré Syndrome (GBS) has occurred within 6 weeks following previous influenza vaccination, the decision to give Fluzone High-Dose should be based on careful consideration of the potential benefits and risks. The 1976 swine influenza vaccine was associated with an elevated risk of GBS. Evidence for a causal relation of GBS with other influenza vaccines is inconclusive; if an excess risk exists, it is probably slightly more than 1 additional case per 1 million persons vaccinated.(See reference 1.)

5.2 Preventing and Managing Allergic Reactions

Appropriate medical treatment must be immediately available to manage potential anaphylactic reactions following administration of Fluzone High-Dose.

5.3 Altered Immunocompetence

If Fluzone High-Dose is administered to immunocompromised persons, including those receiving immunosuppressive therapy, the expected immune response may not be obtained.

5.4 Limitations of Vaccine Effectiveness

Vaccination with Fluzone High-Dose may not protect all recipients.

5.5 Syncope

Syncope (fainting) has been reported following vaccination with Fluzone High-Dose. Procedures should be in place to avoid injury from fainting.

6 ADVERSE REACTIONS

In adults ≥65 years of age, the most common (>10%) injection-site adverse reaction was pain (>35.6%); the most common solicited systemic adverse reactions were myalgia (21.4%), malaise (18.0%), and headache (16.8%).

6.1 Clinical Trials Experience

Because clinical trials are conducted under widely varying conditions, adverse event rates observed in the clinical trial(s) of a vaccine cannot be directly compared to rates in the clinical trial(s) of another vaccine and may not reflect the rates observed in practice. Two clinical studies have evaluated the safety of Fluzone High-Dose.

Study 1 (NCT00391053) was a multi-center, double-blind trial conducted in the US. In this study, adults 65 years of age and older were randomized to receive either Fluzone High-Dose or Fluzone (2006–2007 formulation). The study compared the safety and immunogenicity of Fluzone High-Dose to those of Fluzone. The safety analysis set included 2573 Fluzone High-Dose recipients and 1260 Fluzone recipients.

Table 1 summarizes solicited injection-site reactions and systemic adverse reactions reported within 7 days post-vaccination via diary cards. Onset was usually within the first 3 days after vaccination and a majority of the reactions resolved within 3 days. Solicited injection-site reactions and systemic adverse reactions were more frequent after vaccination with Fluzone High-Dose compared to Fluzone.

Table 1: Frequency of Solicited Injection-Site Reactions and Systemic Adverse Reactions Within 7 Days After Vaccination with Fluzone High-Dose or Fluzone, Adults 65 Years of Age and Older (Study 1 [NCT00391053])
 | Fluzone High-Dose (N [N is the number of vaccinated participants with available data for the reactions listed] =2569–2572) Percentage |  |  | Fluzone (N=1258–1260) Percentage
 | Any | Moderate [Moderate - Injection-site pain: sufficiently discomforting to interfere with normal behavior or activities; Injection- site erythema and Injection-site swelling: ≥2.5 cm to <5 cm; Fever: >100.4°F to ≤102.2°F; Myalgia, Malaise, and Headache: interferes with daily activities] | Severe [Severe - Injection-site pain: incapacitating, unable to perform usual activities; Injection-site erythema and Injection- site swelling: ≥5 cm; Fever: >102.2°F; Myalgia, Malaise, and Headache: prevents daily activities] | Any | Moderate | Severe
Injection-Site Pain | 35.6 | 3.7 | 0.3 | 24.3 | 1.7 | 0.2
Injection-Site Erythema | 14.9 | 1.9 | 1.8 | 10.8 | 0.8 | 0.6
Injection-Site Swelling | 8.9 | 1.6 | 1.5 | 5.8 | 1.3 | 0.6
Myalgia | 21.4 | 4.2 | 1.6 | 18.3 | 3.2 | 0.2
Malaise | 18.0 | 4.7 | 1.6 | 14.0 | 3.7 | 0.6
Headache | 16.8 | 3.1 | 1.1 | 14.4 | 2.5 | 0.3
Fever [Fever - The percentage of temperature measurements that were taken by oral route or not recorded were 97.9% and 2.1%, respectively, for Fluzone High-Dose; and 98.6% and 1.4%, respectively, for Fluzone] (≥99.5°F) | 3.6 | 1.1 | 0.0 | 2.3 | 0.2 | 0.1

Within 6 months post-vaccination, 156 (6.1%) Fluzone High-Dose recipients and 93 (7.4%) Fluzone recipients experienced a serious adverse event (SAE). No deaths were reported within 28 days post-vaccination. A total of 23 deaths were reported during Days 29 – 180 post-vaccination:

16 (0.6%) among Fluzone High-Dose recipients and 7 (0.6%) among Fluzone recipients. The majority of these participants had a medical history of cardiac, hepatic, neoplastic, renal, and/or respiratory diseases. These data do not provide evidence for a causal relationship between deaths and vaccination with Fluzone High-Dose.

Study 2 (NCT01427309) was a multi-center, double-blind post- licensure efficacy trial conducted in the US and Canada over two influenza seasons. In this study, adults 65 years of age and older were randomized to receive either Fluzone High-Dose or Fluzone (2011–2012 and 2012–2013 formulations). The study compared the efficacy and safety of Fluzone High-Dose to those of Fluzone. The safety analysis set included 15,992 Fluzone High-Dose recipients and 15,991 Fluzone recipients.

Within the study surveillance period (approximately 6 to 8 months post-vaccination), 1323 (8.3%) Fluzone High-Dose recipients and 1442 (9.0%) Fluzone recipients experienced an SAE. Within 30 days post-vaccination, 204 (1.3%) Fluzone High-Dose recipients and 200 (1.3%) Fluzone recipients experienced an SAE. The majority of these participants had one or more chronic comorbid illnesses. A total of 167 deaths were reported within 6 to 8 months post-vaccination: 83 (0.5%) among Fluzone High-Dose recipients and 84 (0.5%) among Fluzone recipients. A total of 6 deaths were reported within 30 days post-vaccination: 6 (0.04%) among Fluzone High-Dose recipients and 0 (0%) among Fluzone recipients. These data do not provide evidence for a causal relationship between deaths and vaccination with Fluzone High-Dose.

6.2 Postmarketing Experience

The following events have been spontaneously reported during the postmarketing use of Fluzone, Fluzone High-Dose, Fluzone Quadrivalent, or Fluzone High-Dose Quadrivalent. Because these events are reported voluntarily from a population of uncertain size, it is not always possible to reliably estimate their frequency or establish a causal relationship to vaccine exposure. Adverse events were included based on one or more of the following factors: severity, frequency of reporting, or strength of evidence for a causal relationship to the vaccine.

- Blood and Lymphatic System Disorders: Thrombocytopenia, lymphadenopathy
- Immune System Disorders: Anaphylaxis, other allergic/hypersensitivity reactions (including urticaria, angioedema)
- Eye Disorders: Ocular hyperemia
- Nervous System Disorders: Guillain-Barré syndrome (GBS), convulsions, febrile convulsions, myelitis (including encephalomyelitis and transverse myelitis), facial palsy (Bell's palsy), optic neuritis/neuropathy, brachial neuritis, syncope (shortly after vaccination), dizziness, paresthesia
- Vascular Disorders: Vasculitis, vasodilatation/flushing
- Respiratory, Thoracic and Mediastinal Disorders: Dyspnea, oropharyngeal pain, rhinorrhea, cough, wheezing, throat tightness
- Skin and Subcutaneous Tissue Disorders: Stevens-Johnson syndrome
- General Disorders and Administration Site Conditions: Pruritus, asthenia/fatigue, pain in extremities, chest pain, chills
- Gastrointestinal Disorders: Vomiting, nausea, diarrhea
- Musculoskeletal and Connective Tissue Disorders: Arthralgia

8 USE IN SPECIFIC POPULATIONS

8.1 Pregnancy

Fluzone High-Dose is not approved for use in persons <65 years of age.

There are limited human data and no animal data available to establish whether there is a vaccine-associated risk with use of Fluzone High-Dose in pregnancy.

8.2 Lactation

Fluzone High-Dose is not approved for use in persons <65 years of age. No human or animal data are available to assess the effects of Fluzone High-Dose on the breastfed infant or on milk production/excretion.

8.4 Pediatric Use

Safety and effectiveness of Fluzone High-Dose in persons <65 years of age have not been established.

8.5 Geriatric Use

Safety, immunogenicity, and efficacy of Fluzone High-Dose have been evaluated in adults 65 years of age and older. [See Adverse Reactions (6.1) and Clinical Studies (14)]

11 DESCRIPTION

Fluzone High-Dose (Influenza Vaccine) for intramuscular use is an inactivated influenza vaccine, prepared from influenza viruses propagated in embryonated chicken eggs. The virus- containing allantoic fluid is harvested and inactivated with formaldehyde. Influenza virus is concentrated and purified in a linear sucrose density gradient solution using a continuous flow centrifuge. The virus is then chemically disrupted using a non-ionic surfactant, octylphenol ethoxylate (Triton® X-100), producing a "split virus". The split virus containing hemagglutinin (HA) antigen is further purified and then suspended in sodium phosphate-buffered isotonic sodium chloride solution. The Fluzone High-Dose process uses an additional concentration factor after the ultrafiltration step to obtain a higher HA antigen concentration. The purified split virus from the three strains included in the vaccine are produced separately and then combined to make the trivalent formulation.

Fluzone High-Dose is an injectable suspension and is a colorless opalescent liquid.

Neither antibiotics nor preservative are used in the manufacture of Fluzone High-Dose.

The Fluzone High-Dose prefilled syringe presentation is not made with natural rubber latex.

Fluzone High-Dose is standardized according to United States Public Health Service requirements and is formulated to contain HA of each of the following three influenza strains recommended for the 2025–2026 influenza season: A/Victoria/4897/2022 IVR-238 (H1N1), A/Croatia/10136RV/2023 X-425A (H3N2), and B/Michigan/01/2021 (a B/Austria/1359417/2021-like virus, B Victoria lineage). The amounts of HA and other ingredients per dose of vaccine are listed in Table 2.

Table 2: Fluzone High-Dose Ingredients
Ingredient | Quantity (per dose)
Ingredient | Fluzone High-Dose 0.5 mL Dose
Active Substance: Split influenza virus, inactivated strains [per United States Public Health Service (USPHS) requirement] : | 180 mcg HA total
A (H1N1) | 60 mcg HA
A (H3N2) | 60 mcg HA
B | 60 mcg HA
Other:
Sodium phosphate-buffered isotonic sodium chloride solution | QS [Quantity Sufficient] to appropriate volume
Formaldehyde | ≤100 mcg
Octylphenol ethoxylate | ≤250 mcg
Gelatin | None
Preservative | None

12 CLINICAL PHARMACOLOGY

12.1 Mechanism of Action

Specific levels of hemagglutination inhibition (HI) antibody titer post-vaccination with inactivated influenza virus vaccines have not been correlated with protection from influenza virus infection. In some human studies, antibody titers ≥1:40 have been associated with protection from influenza illness in up to 50% of participants. (See references 2 and 3.)

Antibodies against one influenza virus type or subtype confer limited or no protection against another. Furthermore, antibodies to one antigenic variant of influenza virus might not protect against a new antigenic variant of the same type or subtype. Frequent development of antigenic variants through antigenic drift is the virologic basis for seasonal epidemics and the reason for the usual change of one or more new strains in each year's influenza vaccine.

13 NON-CLINICAL TOXICOLOGY

13.1 Carcinogenesis, Mutagenesis, Impairment of Fertility

Fluzone High-Dose has not been evaluated for carcinogenic or mutagenic potential or for impairment of fertility.

14 CLINICAL STUDIES

14.1 Immunogenicity of Fluzone High-Dose in Adults 65 Years of Age and Older

Study 1 was a multi-center, double-blind pre-licensure trial conducted in the US in which adults 65 years of age and older were randomized to receive either Fluzone High-Dose or Fluzone (2006–2007 formulation). The study compared the safety and immunogenicity of Fluzone High-Dose to those of Fluzone. For immunogenicity analyses, 2576 participants were randomized to Fluzone High-Dose and 1275 participants were randomized to Fluzone. Females accounted for 51.3% of participants in the Fluzone High-Dose group and 54.7% of participants in the Fluzone group. In both groups, the mean age was 72.9 years (ranged from 65 through 97 years in the Fluzone High-Dose group and 65 through 94 years in the Fluzone group); 35% of participants in the Fluzone High-Dose group and 36% of participants in the Fluzone group were 75 years of age or older. Most participants in the Fluzone High-Dose and Fluzone groups, respectively, were White (91.7% and 92.9%), followed by Hispanic (4.8% and 3.7%), and Black (2.7% and 2.7%).

The primary endpoints of the study were HI GMTs and seroconversion rates 28 days after vaccination. Pre-specified statistical superiority criteria required that the lower limit (LL) of the 2- sided 95% CI of the GMT ratio (Fluzone High-Dose/Fluzone) be greater than 1.50 for at least two of the strains, and if one strain failed, non-inferiority of that strain must be demonstrated (LL>0.67), and that the lower limit of the 2-sided 95% CI of the seroconversion rate difference (Fluzone High-Dose minus Fluzone) be greater than 10% for at least two of the strains, and if one strain failed, non-inferiority of that strain must be demonstrated (LL>-10%). As shown in Table 3, statistically superior HI GMTs and seroconversion rates after vaccination with Fluzone High-Dose compared to Fluzone were demonstrated for influenza A subtypes, A (H1N1) and A (H3N2), but not for influenza type B. For strain B, non-inferiority of Fluzone High-Dose compared to Fluzone was demonstrated for both the HI GMTs and seroconversion rates.

Table 3: Post-Vaccination HI Antibody GMTs and Seroconversion Rates and Analyses of Superiority of Fluzone High-Dose Relative to Fluzone, Adults 65 Years of Age and Older (Study 1 [NCT00391053])
Influenza Strain | GMT |  | GMT Ratio | Seroconversion % [Seroconversion: Paired samples with pre-vaccination HI titer <1:10 and post-vaccination (day 28) titer ≥1:40 or a minimum 4-fold increase for participants with pre-vaccination titer ≥1:10] |  | Difference | Met Both Pre-defined Superiority Criteria [Predefined superiority criterion for seroconversion: the lower limit of the two-sided 95% CI of the difference of the seroconversion rates (Fluzone High-Dose minus Fluzone) is >10%. Predefined superiority criterion for the GMT ratio: the lower limit of the 95% CI of the GMT ratio (Fluzone High-Dose divided by Fluzone) is >1.5]
Influenza Strain | Fluzone High-Dose N [N is the number of vaccinated participants with available data for the immunologic endpoint listed] =2542–2544 | Fluzone N=1252 | Fluzone High-Dose over Fluzone (95% CI) | Fluzone High-Dose N=2529–2531 | Fluzone N=1248–1249 | Fluzone High-Dose minus Fluzone (95% CI) | Met Both Pre-defined Superiority Criteria [Predefined superiority criterion for seroconversion: the lower limit of the two-sided 95% CI of the difference of the seroconversion rates (Fluzone High-Dose minus Fluzone) is >10%. Predefined superiority criterion for the GMT ratio: the lower limit of the 95% CI of the GMT ratio (Fluzone High-Dose divided by Fluzone) is >1.5]
A (H1N1) | 115.8 | 67.3 | 1.7 (1.6; 1.8) | 48.6 | 23.1 | 25.4 (22.4; 28.5) | Yes
A (H3N2) | 608.9 | 332.5 | 1.8 (1.7; 2.0) | 69.1 | 50.7 | 18.4 (15.1; 21.7) | Yes
B | 69.1 | 52.3 | 1.3 (1.2; 1.4) | 41.8 | 29.9 | 11.8 (8.6; 15.0) | No

14.2 Efficacy of Fluzone High-Dose in Adults 65 Years of Age and Older

Study 2 was a multi-center, double-blind post-licensure efficacy trial conducted in the US and Canada in which adults 65 years of age and older were randomized (1:1) to receive either Fluzone High-Dose or Fluzone. The study was conducted over two influenza seasons (2011–2012 and 2012–2013); 53% of participants enrolled in the first year of the study were re- enrolled and re-randomized in the second year. The per-protocol analysis set for efficacy assessments included 15,892 Fluzone High-Dose recipients and 15,911 Fluzone recipients. The majority (67%) of participants in the per-protocol analysis set for efficacy had one or more high- risk chronic comorbid conditions.

In the per-protocol analysis set, females accounted for 57.2% of participants in the Fluzone High- Dose group and 56.1% of participants in the Fluzone group. In both groups, the median age was 72.2 years (range 65 through 100 years). Overall, most participants in the study were White (95%); approximately 4% of study participants were Black, and approximately 6% reported Hispanic ethnicity.

The primary endpoint of the study was the occurrence of laboratory-confirmed influenza (as determined by culture or polymerase chain reaction) caused by any influenza viral type/subtype in association with influenza-like illness (ILI), defined as the occurrence of at least one of the following respiratory symptoms: sore throat, cough, sputum production, wheezing, or difficulty breathing; concurrent with at least one of the following systemic signs or symptoms: temperature >99.0°F, chills, tiredness, headaches or myalgia. Participants were monitored for the occurrence of a respiratory illness by both active and passive surveillance, starting 2 weeks post-vaccination for approximately 7 months. After an episode of respiratory illness, nasopharyngeal swab samples were collected for analysis; attack rates and vaccine efficacy were calculated (see Table 4).

Table 4: Relative Efficacy Against Laboratory-Confirmed Influenza [Laboratory-confirmed: culture- or polymerase-chain-reaction-confirmed] Regardless of Similarity to the Vaccine Components, Associated with Influenza-Like Illness [Occurrence of at least one of the following respiratory symptoms: sore throat, cough, sputum production, wheezing, or difficulty breathing; concurrent with at least one of the following systemic signs or symptoms: temperature >99.0°F, chills, tiredness, headaches or myalgia] , Adults 65 Years of Age and Older (Study 2 [NCT01427309])
 | Fluzone High-Dose N [N is the number of vaccinated participants in the per-protocol analysis set for efficacy assessments] =15,892 n [n is the number of participants with protocol-defined influenza-like illness with laboratory confirmation] (%) | Fluzone N=15,911 n (%) | Relative Efficacy % (95% CI)
Any type/subtype [Primary endpoint] | 227 (1.43) | 300 (1.89) | 24.2 (9.7; 36.5) [The pre-specified statistical superiority criterion for the primary endpoint (lower limit of the 2-sided 95% CI of the vaccine efficacy of Fluzone High-Dose relative to Fluzone > 9.1%) was met.]
Influenza A | 190 (1.20) | 249 (1.56) | 23.6 (7.4; 37.1)
A (H1N1) | 8 (0.05) | 9 (0.06) | 11.0 (-159.9; 70.1)
A (H3N2) | 171 (1.08) | 222 (1.40) | 22.9 (5.4; 37.2)
Influenza B [In the first year of the study the influenza B component of the vaccine and the majority of influenza B cases were of the Victoria lineage; in the second year the influenza B component of the vaccine and the majority of influenza B cases were of the Yamagata lineage] | 37 (0.23) | 51 (0.32) | 27.4 (-13.1; 53.8)

A secondary endpoint of the study was the occurrence of culture-confirmed influenza caused by viral types/subtypes antigenically similar to those contained in the respective annual vaccine formulations in association with a modified CDC-defined ILI, defined as the occurrence of a temperature >99.0°F (>37.2°C) with cough or sore throat. The efficacy of Fluzone High-Dose relative to Fluzone for this endpoint was 51.1% (95% CI: 16.8; 72.0).

15 REFERENCES

1 Lasky T, Terracciano GJ, Magder L, et al. The Guillain-Barré syndrome and the 1992–1993 and 1993–1994 influenza vaccines. N Engl J Med 1998;339:1797–802.
2 Hannoun C, Megas F, Piercy J. Immunogenicity and protective efficacy of influenza vaccination. Virus Res 2004;103:133–138.
3 Hobson D, Curry RL, Beare AS, Ward-Gardner A. The role of serum haemagglutination- inhibiting antibody in protection against challenge infection with influenza A2 and B viruses. J Hyg Camb 1972;70:767–777.

16 HOW SUPPLIED/STORAGE AND HANDLING

16.1 How Supplied

Single-dose, prefilled syringe, without needle, 0.5 mL (NDC 49281-125-88) (not made with natural rubber latex). Supplied as a package (NDC 49281-125-65) of 10 prefilled syringes presented as:

- 2 rows of 5 single-dose prefilled syringes separated by a cardboard partition. Use one syringe per dose, or
- 5 sleeves, with each sleeve containing 2 single-dose prefilled syringes. Use one syringe per dose.

16.2 Storage and Handling

Store Fluzone High-Dose refrigerated at 2° to 8°C (35° to 46°F). DO NOT FREEZE. Discard if vaccine has been frozen.

Do not use after the expiration date shown on the label.

17 PATIENT COUNSELING INFORMATION

See FDA-approved patient labeling (Patient Information).

- Inform the patient or caregiver that Fluzone High-Dose contains killed viruses and cannot cause influenza.
- Fluzone High-Dose stimulates the immune system to produce antibodies that help protect against influenza.
- Instruct that annual influenza vaccination is recommended.
- Instruct vaccine recipients and caregivers to report adverse reactions to their healthcare provider and/or to Vaccine Adverse Event Reporting System (VAERS).
- Give the Vaccine Information Statements to recipients or caregivers, which are required by the National Childhood Vaccine Injury Act of 1986 prior to each immunization. These materials are available free of charge at the Centers for Disease Control and Prevention (CDC) website (www.cdc.gov/vaccines).

Fluzone is a registered trademark of Sanofi Pasteur Inc.

Manufactured by:
Sanofi Pasteur Inc.
Swiftwater, PA 18370 USA

Patient Information Sheet
Fluzone® High-Dose
Influenza Vaccine

Please read this information sheet before getting Fluzone High-Dose vaccine. This summary is not intended to take the place of talking with your healthcare provider. If you have questions or would like more information, please talk with your healthcare provider.

What is Fluzone High-Dose vaccine?

Fluzone High-Dose is a vaccine that helps protect against influenza illness (flu).

Fluzone High-Dose vaccine is for people 65 years of age and older.

Vaccination with Fluzone High-Dose vaccine may not protect all people who receive the vaccine.

Who should not get Fluzone High-Dose vaccine?

You should not get Fluzone High-Dose vaccine if you:

- ever had a severe allergic reaction to eggs or egg products.
- ever had a severe allergic reaction after getting any influenza vaccine.

Tell your healthcare provider if you have or have had:

- Guillain-Barré syndrome (severe muscle weakness) after getting an influenza vaccine.
- problems with your immune system as the immune response may be diminished.

How is Fluzone High-Dose vaccine given?

Fluzone High-Dose vaccine is given as an injection into the muscle.

What are the possible side effects of Fluzone High-Dose vaccine?

The most common side effects of Fluzone High-Dose vaccine are:

- pain, redness, and swelling where you got the injection
- muscle ache
- tiredness
- headache

These are not all of the possible side effects of Fluzone High-Dose vaccine. Ask your healthcare provider about other side effects.

Call your healthcare provider for advice about any side effects that concern you. You may report side effects to the Vaccine Adverse Event Reporting System (VAERS) at 1-800-822-7967 or https://vaers.hhs.gov.

Why should I get Fluzone High-Dose vaccine instead of Fluzone vaccine?

An efficacy study in adults 65 years of age and older has demonstrated that Fluzone High-Dose vaccine offers better protection against influenza than Fluzone vaccine.

What are the ingredients in Fluzone High-Dose vaccine?

Fluzone High-Dose vaccine contains 3 killed influenza virus strains. There is no live influenza virus in Fluzone High-Dose. Fluzone High-Dose cannot cause influenza.

Other ingredients include formaldehyde and octylphenol ethoxylate.

Manufactured by: Sanofi Pasteur Inc.
Swiftwater, PA 18370 USA

PRINCIPAL DISPLAY PANEL - 0.5 mL Syringe Label

934378

Lot XXXXXXX
EXP XXXX/XX

NDC 49281-125-88

Influenza Vaccine

Fluzone® High-Dose

2025-2026 Formula

No Preservative

0.5 mL Single-Dose
For IM Use

For 65 yrs of age and older

Mfd by: Sanofi Pasteur Inc.

Rx only

PRINCIPAL DISPLAY PANEL - 0.5 mL Syringe Package

NDC 49281-125-65

2025-2026
Formula

Influenza Vaccine
Fluzone® High-Dose

Rx only

FOR ADULTS
65^+

For Intramuscular Use
10 single-dose prefilled syringes 0.5 mL each

sanofi